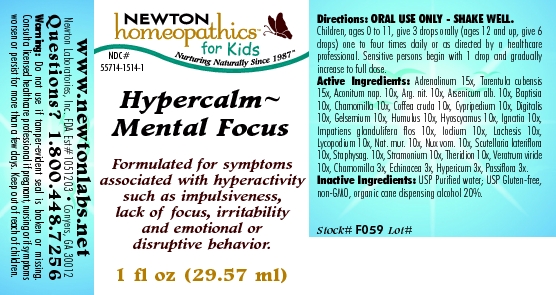 DRUG LABEL: Hypercalm - Mental Focus 
NDC: 55714-1514 | Form: LIQUID
Manufacturer: Newton Laboratories, Inc.
Category: homeopathic | Type: HUMAN OTC DRUG LABEL
Date: 20110301

ACTIVE INGREDIENTS: Epinephrine 15 [hp_X]/1 mL; Citharacanthus Spinicrus 15 [hp_X]/1 mL; Aconitum Napellus 10 [hp_X]/1 mL; Silver Nitrate 10 [hp_X]/1 mL; Arsenic Trioxide 10 [hp_X]/1 mL; Baptisia Tinctoria 10 [hp_X]/1 mL; Matricaria Recutita 10 [hp_X]/1 mL; Arabica Coffee Bean 10 [hp_X]/1 mL; Cypripedium Parvifolum Root 10 [hp_X]/1 mL; Digitalis 10 [hp_X]/1 mL; Gelsemium Sempervirens Root 10 [hp_X]/1 mL; Hops 10 [hp_X]/1 mL; Hyoscyamus Niger 10 [hp_X]/1 mL; Strychnos Ignatii Seed 10 [hp_X]/1 mL; Impatiens Glandulifera Flower 10 [hp_X]/1 mL; Iodine 10 [hp_X]/1 mL; Lachesis Muta Venom 10 [hp_X]/1 mL; Lycopodium Clavatum Spore 10 [hp_X]/1 mL; Sodium Chloride 10 [hp_X]/1 mL; Strychnos Nux-vomica Seed 10 [hp_X]/1 mL; Scutellaria Lateriflora 10 [hp_X]/1 mL; Delphinium Staphisagria Seed 10 [hp_X]/1 mL; Datura Stramonium 10 [hp_X]/1 mL; Theridion Curassavicum 10 [hp_X]/1 mL; Veratrum Viride Root 10 [hp_X]/1 mL; Echinacea, Unspecified 3 [hp_X]/1 mL; Hypericum Perforatum 3 [hp_X]/1 mL; Passiflora Incarnata Flowering Top 3 [hp_X]/1 mL
INACTIVE INGREDIENTS: Alcohol

Hypercalm - Mental Focus

INDICATIONS & USAGE SECTION

Hypercalm - Mental Focus Formulated for symptoms associated with hyperactivity such as impulsiveness, lack of focus, irritability and emotional or disruptive behavior.

DOSAGE & ADMINISTRATION SECTION

ORAL USE ONLY - SHAKE WELL. Children, ages 0 to 11, give 3 drops orally (ages 12 and up, give 6 drops) one to four times daily or as directed by a healthcare professional. Sensitive persons begin with 1 drop and gradually increase to full dose.

OTC - ACTIVE INGREDIENT SECTION

Adrenalinum 15x, Tarentula cubensis 15x, Aconitum nap. 10x, Arg. nit. 10x, Arsenicum alb. 10x, Baptisia 10x, Chamomilla 10x, Coffea cruda 10x, Cypripedium 10x, Digitalis 10x, Gelsemium 10x, Humulus 10x, Hyoscyamus 10x, Ignatia 10x, Impatiens glandulifera flos 10x, Iodium 10x, Lachesis 10x, Lycopodium 10x, Nat. mur. 10x, Nux vom. 10x, Scutellaria lateriflora 10x, Staphysag. 10x, Stramonium 10x, Theridion 10x, Veratrum viride 10x, Chamomilla 3x, Echinacea 3x, Hypericum 3x, Passiflora 3x.

OTC - PURPOSE SECTION

Formulated for symptoms associated with hyperactivity such as impulsiveness, lack of focus, irritability and emotional or disruptive behavior.

INACTIVE INGREDIENT SECTION

Inactive Ingredients: USP Purified Water; USP Gluten-free, non-GMO, organic cane dispensing alcohol 20%.

QUESTIONS SECTION

www.newtonlabs.net Newton Laboratories, Inc. FDA Est # 1051203 - Conyers, GA30012
Questions? 1.800.448.7256

WARNINGS SECTION

Warning: Do not use if tamper - evident seal is broken or missing. Consult a licensed healthcare professional if pregnant, nursing or if symptoms worsen or persist for more than a few days. Keep out of reach of children.

OTC - PREGNANCY OR BREAST FEEDING SECTION

Consult a licensed healthcare professional if pregnant, nursing or if symptoms worsen or persist for more than a few days.

OTC - KEEP OUT OF REACH OF CHILDREN SECTION

Keep out of reach of children.